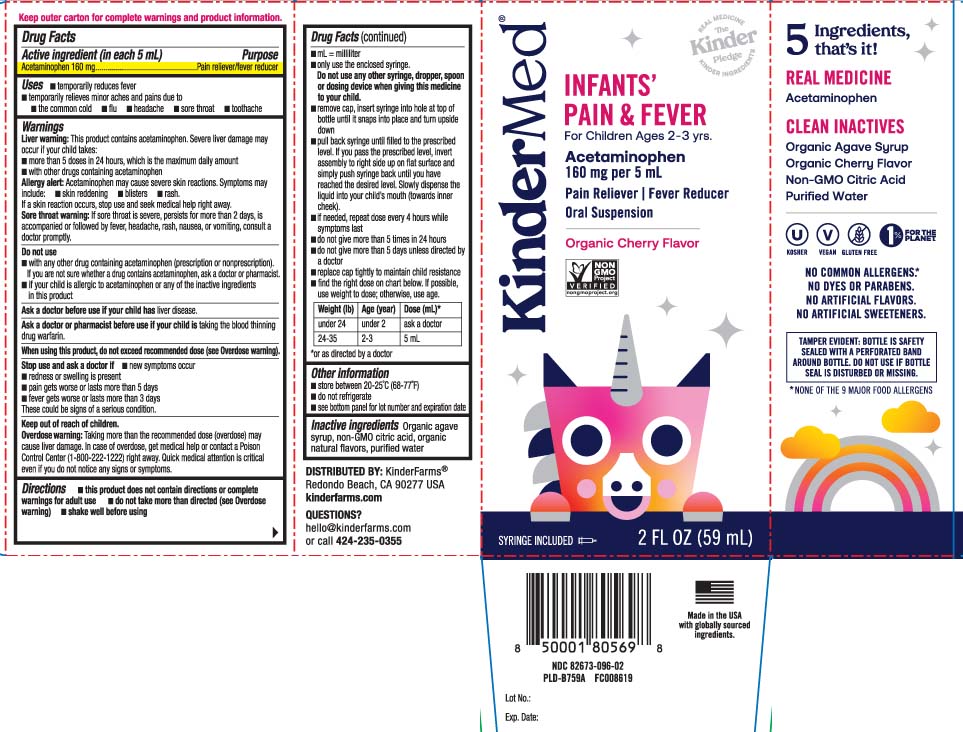 DRUG LABEL: Infants Pain and Fever
NDC: 82673-096 | Form: SUSPENSION
Manufacturer: KinderFarms, LLC
Category: otc | Type: HUMAN OTC DRUG LABEL
Date: 20250108

ACTIVE INGREDIENTS: ACETAMINOPHEN 160 mg/5 mL
INACTIVE INGREDIENTS: AGAVE TEQUILANA JUICE; WATER; CITRIC ACID MONOHYDRATE

Drug Facts

Active ingredient (in each 5 mL)

Acetaminophen 160 mg

Purpose

Pain reliever/fever reducer

Uses

- temporarily reduces fever
- temporarily relieves minor aches and pains due to
  - the common cold
  - flu
  - headache
  - sore throat
  - toothache

Warnings

Liver warning: This product contains acetaminophen. Severe liver damage may occur if your child takes:

- more than 5 doses in 24 hours, which is the maximum daily amount
- with other drugs containing acetaminophen

Allergy alert: Acetaminophen may cause severe skin reactions. symptoms may include:

- skin reddening
- blisters
- rash

If a skin reaction occurs, stop use and seek medical help right away

Sore throat warning: If sore throat is severe, persists for more than 2 days, is accompanied or followed by fever, headache, rash, nausea, or vomiting, consult a doctor promptly.

Do not use

- with any other drug containing acetaminophen (prescription or non prescription). If you are not sure whether a drug contains acetaminophen, ask a doctor or pharmacist.
- if your child is allergic to acetaminophen or any of the inactive ingredients in this product.

Ask a doctor before use if your child has

liver disease.

Ask a doctor or pharmacist before use if your child is

taking the blood thinning drug warfarin.

When using this product,

do not exceed recommended dose (see overdose warning)

Stop use and ask a doctor if

- new symptoms occur
- redness or swelling is present
- pain gets worse or lasts more than 5 days
- fever gets worse or lasts more than 3 days

These could be signs of a serious condition.

Keep out of reach of children.

Overdose warning: Taking more than the recommended dose (overdose) may cause liver damage. In case of overdose, get medical help or contact a Poison Control Center (1-800-222-1222) right away. Quick medical attention is critical even if you do not notice any signs or symptoms.

Directions

- this product does not contain directions or complete warnings for adult use.
- do not take more than directed (see overdose warning)
- shake well before using
- mL= milliliter
- only use the enclosed syringe. Do not use any other syringe, dropper, spoon or dosing device when giving this medicine to your child
- remove cap, insert syringe into hole at top of bottle until it snaps into place and turn upside down
- pull back syringe until filled to be prescribed level. If you pass the prescribed level, invert assembly to right side up on flat surface and simply push syringe back until you have reached the desired level. Slowly dispense the liquid into your child's mouth (towards inner cheek)
- If needed, repeat dose every 4 hours while symptoms last
- do not give more than 5 times in 24 hours
- do not give more than 5 days unless directed by a doctor
- replace cap tightly to maintain child resistance
- find the right dose on chart below. If possible, use weight to dose; otherwise, use age

Weight (lb) | Age (year) | Dose (mL)*
under 24 | under 2 years | ask a doctor
24-35 | 2-3 years | 5 mL

*or as directed by a doctor

Other information

- store between 20-25ºC (68º-77ºF)
- do not refrigerate.
- see bottom panel for lot number and expiration date

Inactive ingredient

Organic agave syrup, non-GMO citric acid, organic natural flavors, purified water

Questions?

Call 424-235-0355

Principal Display Panel

INFANTS' PAIN & FEVER

For Children Ages 2-3 yrs

Acetaminophen

160 mg per 5 mL

Pain Reliever | Fever Reducer

Oral Suspension

Organic Cherry Flavor

SYRINGE INCLUDED

FL OZ (mL)

Keep outer carton for complete warnings and product information.

TAMPER EVIDENT: BOTTLE IS SAFETY SEALED WITH A PERFORATED BAND AROUND BOTTLE. DO NOT USE IF BOTTLE SEAL IS DISTURBED OR MISSING.

DISTRIBUTED BY: KinderFarms®

Redondo Beach, CA 90277 USA

kinderfarms.com

Package Label

KINDERMED Infants' Pain & Fever Cherry Flavor